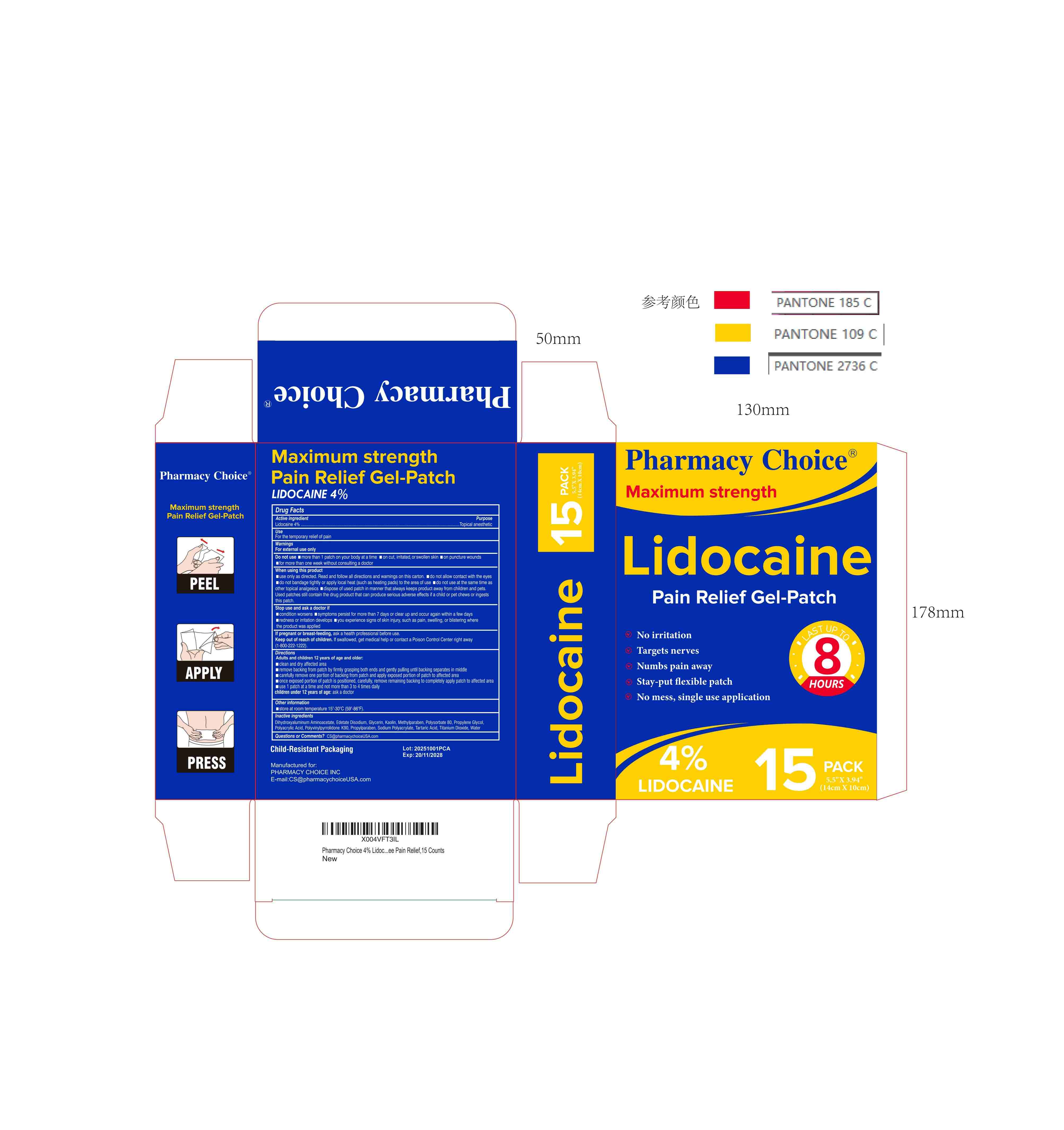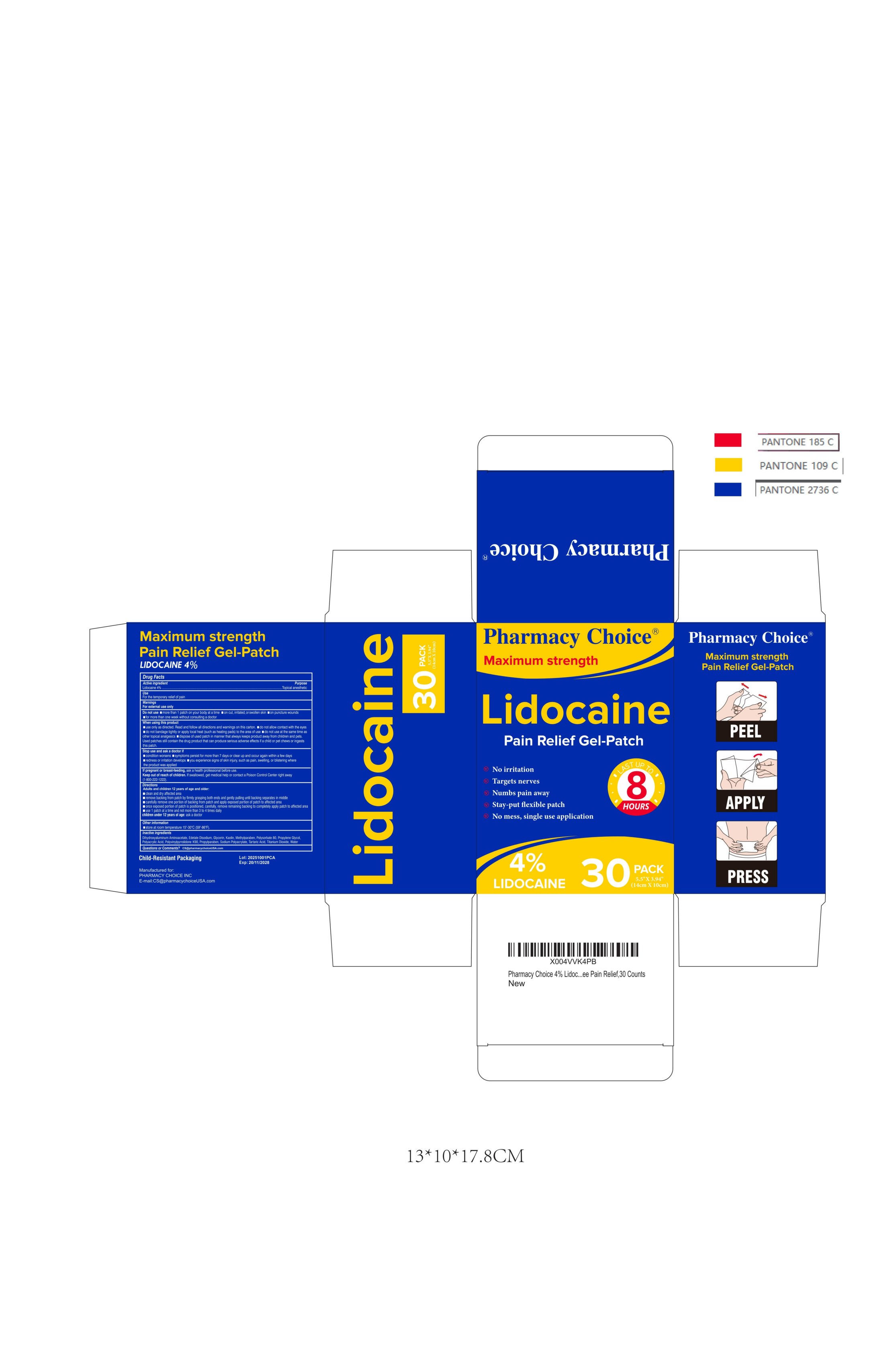 DRUG LABEL: PAIN RELIEVING
NDC: 84007-160 | Form: PATCH
Manufacturer: Medhome Pharma Inc
Category: otc | Type: HUMAN OTC DRUG LABEL
Date: 20251022

ACTIVE INGREDIENTS: LIDOCAINE 0.04 g/1 g
INACTIVE INGREDIENTS: METHYLPARABEN; TITANIUM DIOXIDE; PROPYLENE GLYCOL; TARTARIC ACID; SODIUM POLYACRYLATE (2500000 MW); WATER; DIHYDROXYALUMINUM AMINOACETATE ANHYDROUS; POLYSORBATE 80; GLYCERIN; POLYACRYLIC ACID (250000 MW); KAOLIN; EDETATE DISODIUM; PROPYLPARABEN; POVIDONE K90

ACTIVE INGREDIENT

Lidocaine 4% ...... Purpose: Topical Anesthetic

PURPOSE

Topical Anesthetic

USE IN SPECIFIC POPULATIONS

For temporary relief of pain

WARNINGS

For external use only

ASK DOCTOR/PHARMACIST

localized skin reactions occur, such as rash, itching, redness, irritation, pain, swelling and blistering
Conditions worsen
Symptoms persists for more than 7 days
Symptoms clear up and occur again within a few days

WHEN USING

Use only as directed
Avoid contact with the eyes, mucous membranes or rashed
Do not bandage tightly

DO NOT USE

More than 1 patch at a time
On wounds or damaged skin
With a heating pad
If you are allergic to any ingredients of this product

STOP USE

localized skin reactions occur, such as rash, itching, redness, irritation, pain, swelling and blistering
Conditions worsen
Symptoms persists for more than 7 days
Symptoms clear up and occur again within a few days

PREGNANCY OR BREAST FEEDING

If pregnant or breastfeeding, ask a health professional before use

Keep out of reach of children. If swallowed, get medical help or contact a Poison Control Center right away.

INDICATIONS AND USAGE

Adult and Children 12 years of age and over:

Clean and dry affected area
Remove film from patch and apply to the skin (see illustration)
Apply 1 patch at a time to affected area, not more than 3 to 4 times daily
Remove patch from the skin after at most 8-hour application

Children under 12 years of age: Consult a doctor

This is a strip, patch dosage form.

The active ingredient strength is 4% w/w.

One patch one time, no more than 8 hours one time.

INACTIVE INGREDIENT

Glycerin, Sodium Polyacrylate, Dihydroxyaluminum Aminoacetate, Disodium Ethylenediaminetetraacetic Acid, Kaolin, Titanium Dioxide, Polysorbate 80, Propylene Glycol, Tartaric Acid, Polyacrylic Acid, Polyvinylpyrrolidone K90, Methylparaben, Propylparaben, Water

QUESTIONS

E-mail：CS@pharmacychoiceUSA.com

OTHER SAFETY INFORMATION

Avoid storing product in direct sunlight
Protect product from excessive moisture